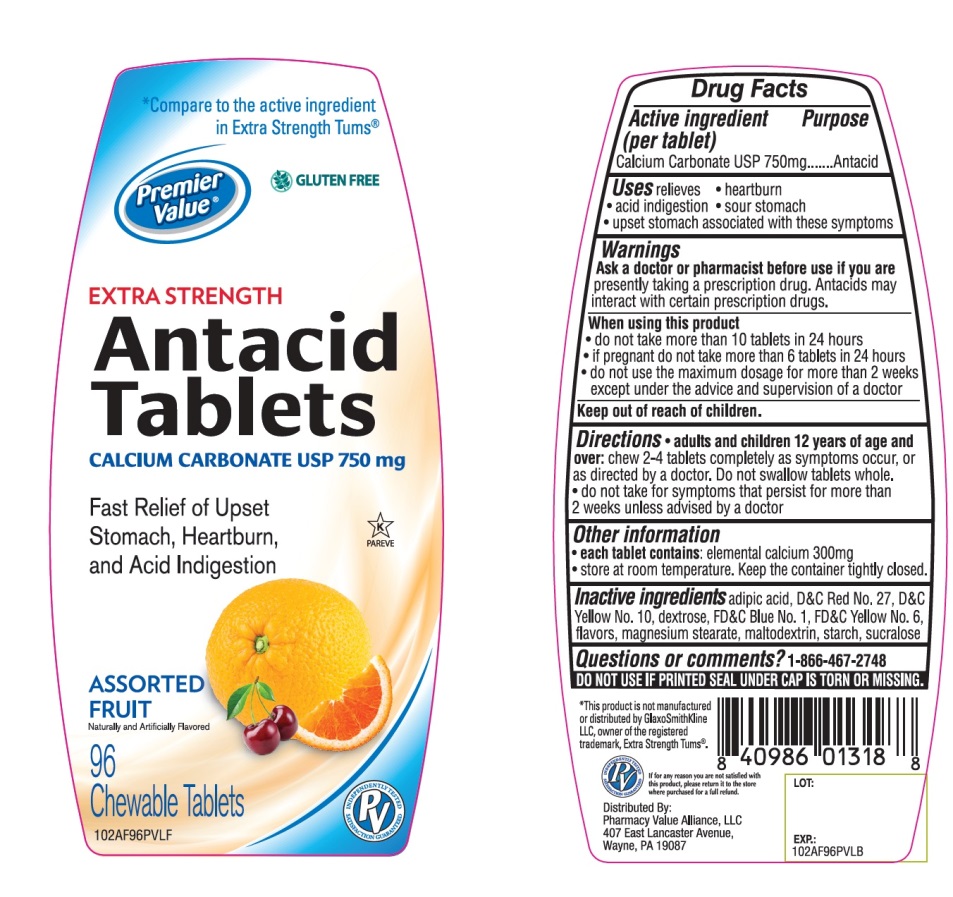 DRUG LABEL: Premier Value Chewable Antacid Extra Strength
NDC: 68016-666 | Form: TABLET, CHEWABLE
Manufacturer: Chain Drug Consortium
Category: otc | Type: HUMAN OTC DRUG LABEL
Date: 20241025

ACTIVE INGREDIENTS: CALCIUM CARBONATE 500 mg/1 1
INACTIVE INGREDIENTS: ADIPIC ACID; FD&C BLUE NO. 1; DEXTROSE, UNSPECIFIED FORM; MAGNESIUM STEARATE; MALTODEXTRIN; D&C RED NO. 27; STARCH, CORN; SUCRALOSE; FD&C YELLOW NO. 6; D&C YELLOW NO. 10

Premier Value Extra Strength Antacid Tablets Drug Facts

Active ingredient

Calcium Carbonate USP 750mg

Purpose

Antacid

Uses

relieves:

• heartburn

• sour stomach

• acid indigestion

• upset stomach associated with these symptoms

Warnings

Ask a doctor or pharmacist before use if you are taking a prescription drug. Antacids may interact with certain prescription drugs.

When using this product

• do not take more than 10 tablets in 24 hours

• if pregnant do not take more than 6 tablets in 24 hours

• do not use the maximum dosage for more than 2 weeks except under the advice and supervision of a doctor.

Directions

• adults and children 12 years of age and over: chew 2-4 tablets completely as symptoms occur, or as directed by a doctor. Do not swallow tablets whole.

• do not use the maximum dosage for more than 2 weeks except under the advice and supervision of a doctor.

Other Information

• each tablets contains: elemental calcium 300mg

• Store at room temperature. Keep the container tightly closed

Inactive ingredients

adipic acid, D&C Red No. 27, D&C Yellow No. 10, dextrose, FD&C Blue No. 1, FD&C Yellow no. 6, flavors, magnesium stearate, maltodextrin, starch, sucralose.

Questions or comments?

1-866-467-2748

SAFETY SEALED: DO NOT USE IF PRINTED SEAL UNDER CAP IS TORN OR MISSING

Package/Label Principal Display Panel

*Compare to the active ingredient in Extra Strength Tums®

Premier Value®

Extra Strength

Calcium Antacid Tablets

ASSORTED FRUIT

Naturally and Artificially Flavored

For Fast Relief of Upset Stomach, Heartburn, Acid Indigestion

96 Chewable Tablets

Distributed by

Pharmacy Value Alliance, LLC

407 East Lancaster Avenue,

Wayne, PA 19087

This product is not manufactured or distributed by GlaxoSmithKline LLC, owner of the registered trademark, Extra Strength Tums®